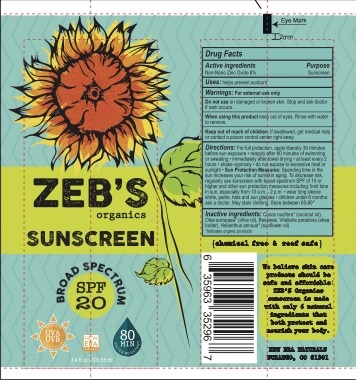 DRUG LABEL: Zebs broad spectrum sunscreen
NDC: 70397-2016 | Form: LOTION
Manufacturer: New Era Naturals LLC
Category: otc | Type: HUMAN OTC DRUG LABEL
Date: 20160129

ACTIVE INGREDIENTS: ZINC OXIDE 8 g/100 g
INACTIVE INGREDIENTS: SUNFLOWER OIL 33 g/100 g; COCONUT OIL 24 g/100 g; WHITE WAX 14 g/100 g; OLIVE OIL 11 g/100 g; SHEA BUTTER 10 g/100 g

Zebs Organics-20 SPF broad spectrum sunscreen